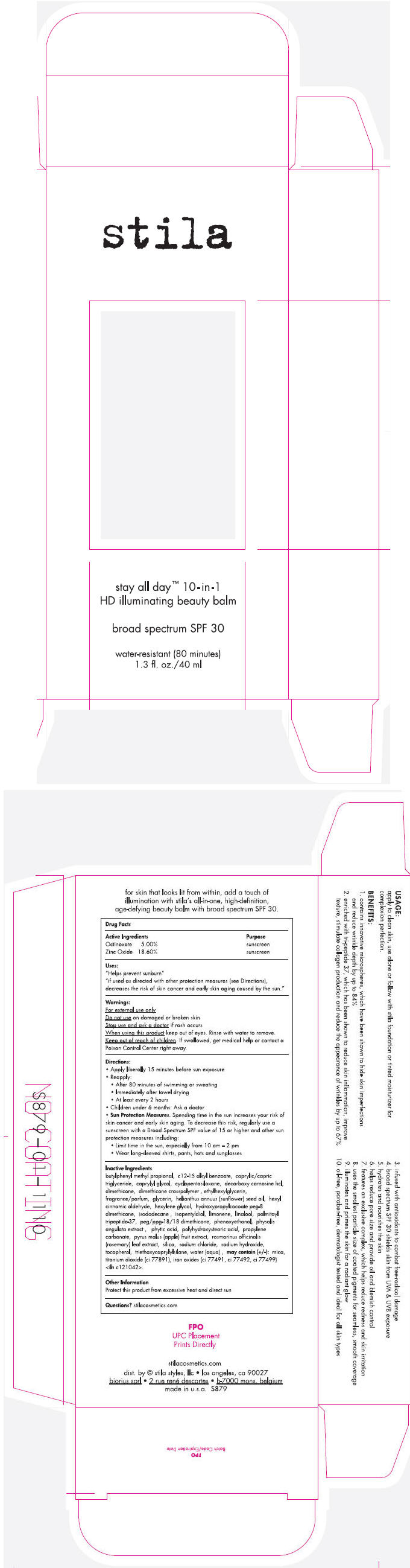 DRUG LABEL: Stila Stay All Day 10-in-1 HD Illuminating Beauty Balm Broad Spectrum SPF 30
NDC: 76049-879 | Form: CREAM
Manufacturer: Stila Styles, LLC
Category: otc | Type: HUMAN OTC DRUG LABEL
Date: 20131125

ACTIVE INGREDIENTS: OCTINOXATE 50 mg/1 mL; ZINC OXIDE 186 mg/1 mL
INACTIVE INGREDIENTS: BUTYLPHENYL METHYLPROPIONAL; ALKYL (C12-15) BENZOATE; MEDIUM-CHAIN TRIGLYCERIDES; CAPRYLYL GLYCOL; CYCLOMETHICONE 5; DECARBOXY CARNOSINE HYDROCHLORIDE; DIMETHICONE; ETHYLHEXYLGLYCERIN; GLYCERIN; SUNFLOWER OIL; .ALPHA.-HEXYLCINNAMALDEHYDE; HEXYLENE GLYCOL; HYDROXYPROPYLCOCOATE PEG-8 DIMETHICONE; ISODODECANE; ISOPENTYLDIOL; LINALOOL, (+/-)-; PEG/PPG-18/18 DIMETHICONE; PHENOXYETHANOL; PHYSALIS ANGULATA; FYTIC ACID; PROPYLENE CARBONATE; APPLE; ROSEMARY; SILICON DIOXIDE; SODIUM CHLORIDE; SODIUM HYDROXIDE; TOCOPHEROL; TRIETHOXYCAPRYLYLSILANE; WATER; MICA; TITANIUM DIOXIDE; FERRIC OXIDE RED; FERRIC OXIDE YELLOW; FERROSOFERRIC OXIDE

Stila Stay All Day™ 10-in-1 HD Illuminating Beauty Balm Broad Spectrum SPF 30

Drug Facts

ACTIVE INGREDIENT

Active Ingredients |  |  | Purpose
Octinoxate | 5.00% |  | sunscreen
Zinc Oxide | 18.60% |  | sunscreen

Uses

"Helps prevent sunburn"

"if used as directed with other protection measures (see Directions), decreases the risk of skin cancer and early skin aging caused by the sun."

Warnings

For external use only

Do not use on damaged or broken skin

Stop use and ask a doctor if rash occurs

When using this product keep out of eyes. Rinse with water to remove.

Keep out of reach of children. If swallowed, get medical help or contact a Poison Control Center right away.

Directions

- Apply liberally 15 minutes before sun exposure
- Reapply:
  - After 80 minutes of swimming or sweating
  - Immediately after towel drying
  - At least every 2 hours
- Children under 6 months: Ask a doctor
- Sun Protection Measures. Spending time in the sun increases your risk of skin cancer and early skin aging. To decrease this risk, regularly use a sunscreen with a Broad Spectrum SPF value of 15 or higher and other sun protection measures including:
  - Limit time in the sun, especially from 10 am – 2 pm
  - Wear long-sleeved shirts, pants, hats and sunglasses

Inactive Ingredients

butylphenyl methyl propional, c12-15 alkyl benzoate, caprylic/capric triglyceride, caprylyl glycol, cyclopentasiloxane, decarboxy carnosine hcl, dimethicone, dimethicone crosspolymer , ethylhexylglycerin, fragrance/parfum, glycerin, helianthus annuus (sunflower) seed oil, hexyl cinnamic aldehyde, hexylene glycol, hydroxypropylcocoate peg-8 dimethicone, isododecane , isopentyldiol, limonene, linalool, palmitoyl tripeptide-37, peg/ppg-18/18 dimethicone, phenoxyethanol, physalis angulata extract , phytic acid, polyhydroxystearic acid, propylene carbonate, pyrus malus (apple) fruit extract, rosmarinus officinalis (rosemary) leaf extract, silica, sodium chloride, sodium hydroxide, tocopherol, triethoxycaprylylsilane, water (aqua) , may contain (+\-): mica, titanium dioxide (ci 77891), iron oxides (ci 77491, ci 77492, ci 77499) <iln c121042>.

Other Information

Protect this product from excessive heat and direct sun

Questions?

stilacosmetics.com

dist. by stila styles, llc • los angeles, ca 90027

PRINCIPAL DISPLAY PANEL - 40 ml Tube Carton

stila

stay all day™ 10-in-1
HD illuminating beauty balm

broad spectrum SPF 30

water-resistant (80 minutes)
1.3 fl. oz./40 ml